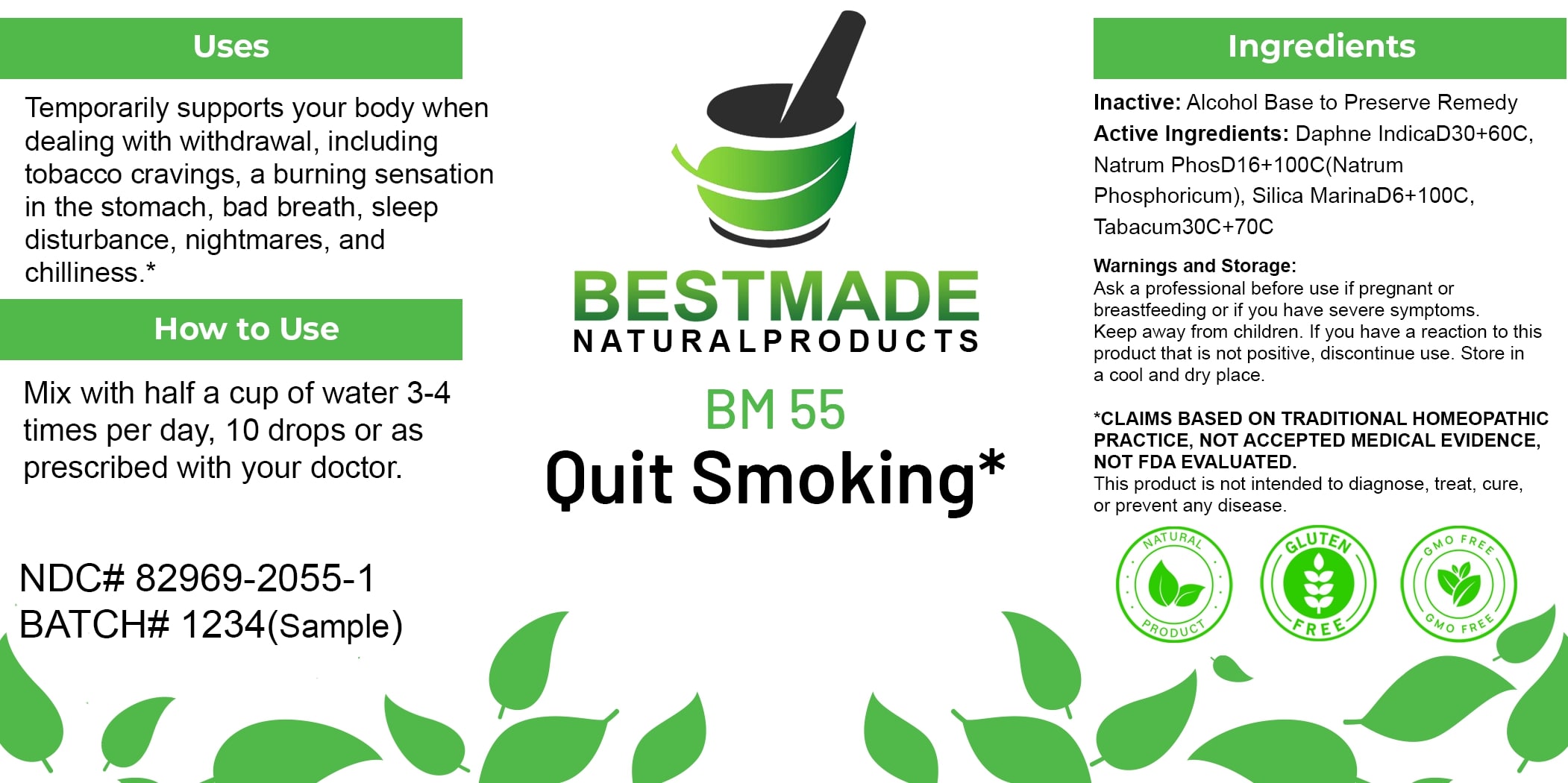 DRUG LABEL: Bestmade Natural Products BM55
NDC: 82969-2055 | Form: LIQUID
Manufacturer: Bestmade Natural Products
Category: homeopathic | Type: HUMAN OTC DRUG LABEL
Date: 20250124

ACTIVE INGREDIENTS: SILICA 100 [hp_C]/100 [hp_C]; DAPHNE ODORA BARK 60 [hp_C]/100 [hp_C]; SODIUM PHOSPHATE, DIBASIC, HEPTAHYDRATE 100 [hp_C]/100 [hp_C]; TOBACCO LEAF 70 [hp_C]/100 [hp_C]
INACTIVE INGREDIENTS: ALCOHOL 100 [hp_C]/100 [hp_C]

BM55

DOSAGE AND ADMINISTRATION

How to Use

Mix with half a cup of water 3-4 times per day, 10 drops or as prescribed with your doctor.

INACTIVE INGREDIENT

Ingredients

Inactive: Alcohol Base to Preserve Remedy

ACTIVE INGREDIENT

Active Ingredients: Daphne Indica D30+60C, Natrum Phos D16+100C (Natrum Phosphoricum), Silica Marina D6+100C, Tabacum 30C+70C

Uses

Temporarily supports your body when dealing with withdrawal, including tobacco cravings, a burning sensation in the stomach, bad breath, sleep disturbance, nightmares, and chilliness.*

*CLAIMS BASED ON TRADITIONAL HOMEOPATHIC PRACTICE, NOT ACCEPTED MEDICAL EVIDENCE. NOT FDA EVALUATED.

This product is not intended to diagnose, treat, cure, or prevent any disease.

Uses

Temporarily supports your body when dealing with withdrawal, including tobacco cravings, a burning sensation in the stomach, bad breath, sleep disturbance, nightmares, and chilliness.*

*CLAIMS BASED ON TRADITIONAL HOMEOPATHIC PRACTICE, NOT ACCEPTED MEDICAL EVIDENCE. NOT FDA EVALUATED.

This product is not intended to diagnose, treat, cure, or prevent any disease.

KEEP OUT OF REACH OF CHILDREN

Warnings and Storage:

Ask a professional before use if pregnant or breastfeeding or if you have severe symptoms. Keep away from children. If you have a reaction to this product that is not positive, discontinue use. Store in a cool and dry place.

Warnings and Storage:

Ask a professional before use if pregnant or breastfeeding or if you have severe symptoms. Keep away from children. If you have a reaction to this product that is not positive, discontinue use. Store in a cool and dry place.

*CLAIMS BASED ON TRADITIONAL HOMEOPATHIC PRACTICE, NOT ACCEPTED MEDICAL EVIDENCE. NOT FDA EVALUATED.

This product is not intended to diagnose, treat, cure, or prevent any disease.

Entire package label